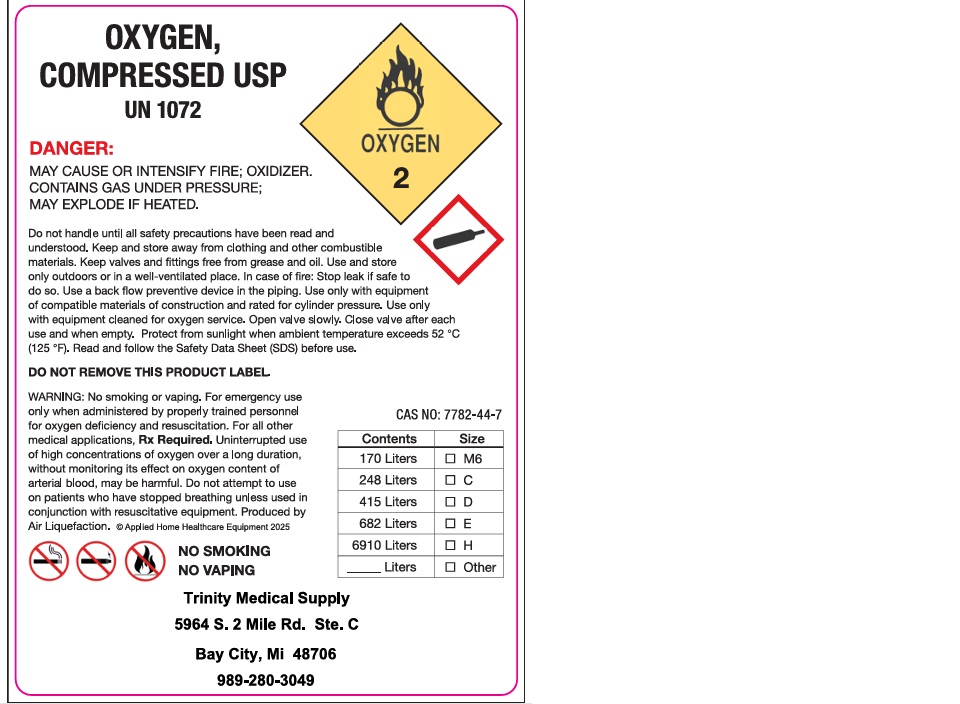 DRUG LABEL: Oxygen
NDC: 73087-001 | Form: GAS
Manufacturer: KENRIC INC dba Trinity Medical Supplies
Category: prescription | Type: HUMAN PRESCRIPTION DRUG LABEL
Date: 20260105

ACTIVE INGREDIENTS: OXYGEN 990 mL/1 L

Oxygen

PACKAGE LABEL

OXYGEN, COMPRESSED USP

UN 1072

DANGER: MAY CAUSE OR INTENSIFY FIRE; OXIDIZER. CONTAINS GAS UNDER PRESSURE; MAY EXPLODE IF HEATED.

Do not handle until all safety precautions have been read and understood. Keep and store away from clothing and other combustible materials. Keep valves and fittings free from grease and oil. Use and store only outdoors or in a well-ventilated place. In case of fire: Stop leak if safe to do so. Use a back flow preventive device in the piping. Use only with equipment of compatible materials of construction and rated for cylinder pressure. Use only with equipment cleaned for oxygen service. Open valve slowly. Close valve after each use and when empty. Protect from sunlight when ambient temperature exceeds 52 C (125 F). Read and follow the Safety Data Sheet (SDS) before use.

DO NOT REMOVE THIS PRODUCT LABEL.

WARNING: No smoking or vaping. For emergency use only when administered by properly trained personnel for oxygen deficiency and resuscitation. For all other medical applications, Rx Required. Uninterrupted use of high concentrations of oxygen over a long duration, without monitoring its effect on oxygen content of arterial blood, may be harmful. Do not attempt to use on patients who have stopped breathing unless used in conjunction with resuscitative equipment. Produced by Air Liquefaction.

NO SMOKING

NO VAPING

Trinity Medical Supply

5964 S. 2 Mile Rd. Ste. C

Bay City, Mi 48706

989-280-3049

CAS NO: 7782-44-7

Contents Size

170 Liters M6

248 Liters C

415 Liters D

682 Liters E

6910 Liters H

Liters Other